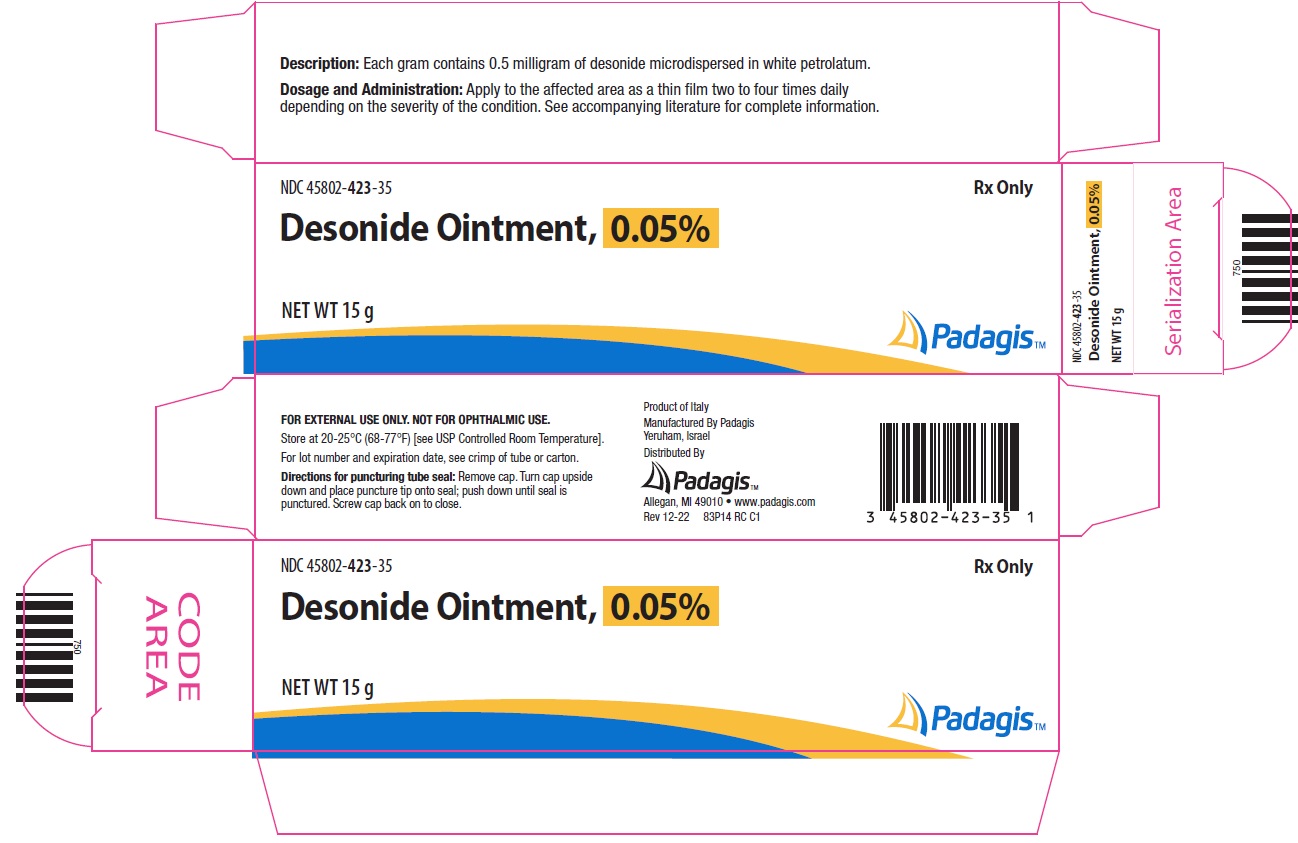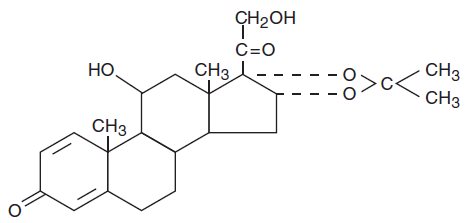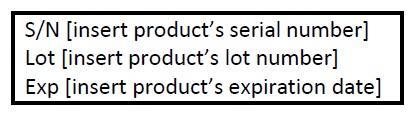 DRUG LABEL: Desonide
NDC: 45802-423 | Form: OINTMENT
Manufacturer: Padagis Israel Pharmaceuticals Ltd
Category: prescription | Type: HUMAN PRESCRIPTION DRUG LABEL
Date: 20221201

ACTIVE INGREDIENTS: DESONIDE 0.5 mg/1 g
INACTIVE INGREDIENTS: PETROLATUM

Desonide Ointment, 0.05%

For Dermatologic Use Only

Not For Ophthalmic Use

Rx Only

DESCRIPTION

Desonide Ointment, 0.05% contains desonide (Pregna-1,4-diene-3,20-dione,11,21-dihydroxy-16,17-[(1-methylethylidene)bis(oxy)]-,(11ß,16α)) a synthetic corticosteroid for topical dermatologic use. The corticosteroids constitute a class of primary synthetic steroids used topically as anti-inflammatory and antipruritic agents.

Chemically, desonide, the active ingredient in Desonide Ointment, 0.05% is C24H32O6. It has the following structural formula:

The molecular weight of desonide is 416.51. It is a white to off-white powder. The solubility of desonide in distilled water saturated with ether is 184 mg/L.

Each gram of Desonide Ointment, 0.05% contains 0.5 milligram of desonide microdispersed in a base of white petrolatum.

CLINICAL PHARMACOLOGY

Like other topical corticosteroids, desonide has anti-inflammatory, antipruritic, and vasoconstrictive properties. The mechanism of the anti-inflammatory activity of the topical steroids, in general, is unclear. However corticosteroids are thought to act by the induction of phospholipase A2 inhibitory proteins, collectively called, lipocortins. It is postulated that these proteins control the biosynthesis of potent mediators of inflammation such as prostaglandins and leukotrienes by inhibiting the release of their common precursor arachidonic acid. Arachidonic acid is released from membrane phospholipids by phospholipase A2.

Pharmacokinetics -

The extent of percutaneous absorption of topical corticosteroids is determined by many factors, including the vehicle and the integrity of the epidermal barrier. Occlusive dressings with hydrocortisone for up to 24 hours have not been demonstrated to increase penetration; however, occlusion of hydrocortisone for 96 hours markedly enhances penetration. Topical corticosteroids can be absorbed from normal intact skin. Inflammation and/or other disease processes in the skin may increase percutaneous absorption.

Studies performed with Desonide Ointment, 0.05% indicate that it is in the low range of potency as compared with other topical corticosteroids.

INDICATIONS AND USAGE

Desonide Ointment, 0.05% is a low potency corticosteroid indicated for the relief of the inflammatory and pruritic manifestations of corticosteroid responsive dermatoses.

It should not be used for longer than two weeks unless directed by a physician.

CONTRAINDICATIONS

Desonide Ointment, 0.05% is contraindicated in those patients with a history of hypersensitivity to any of the components of the preparation.

PRECAUTIONS

General -

Systemic absorption of topical corticosteroids can produce reversible hypothalamic-pituitary-adrenal (HPA) axis suppression with the potential for glucocorticosteroid insufficiency after withdrawal of treatment. Manifestations of Cushing's syndrome, hyperglycemia, and glucosuria can also be produced in some patients by systemic absorption of topical corticosteroids while on treatment.

Patients applying a topical steroid to a large surface area or to areas under occlusion should be evaluated periodically for evidence of HPA axis suppression. This may be done by using the ACTH stimulation, A.M. plasma cortisol, and urinary free cortisol tests. Patients receiving superpotent corticosteroids should not be treated for more than two weeks at a time and only small areas should be treated at any one time due to the increased risk of HPA suppressions.

No specific studies relevant to potential HPA suppression have been conducted with Desonide Ointment, 0.05%.

If HPA axis suppression is noted, an attempt should be made to withdraw the drug, to reduce the frequency of application, or to substitute a less potent corticosteroid. Recovery of HPA axis function is generally prompt upon discontinuation of topical corticosteroids. Infrequently, signs and symptoms of glucocorticosteroid insufficiency may occur requiring supplemental systemic corticosteroids. For information on systemic supplementation, see prescribing information for those products.

Pediatric patients may be more susceptible to systemic toxicity from equivalent doses due to their larger skin surface to body mass ratios (see PRECAUTIONS - Pediatric Use).

If irritation develops, Desonide Ointment, 0.05% should be discontinued and appropriate therapy instituted. Allergic contact dermatitis with corticosteroids is usually diagnosed by observing a failure to heal rather than noting a clinical exacerbation as with most topical products not containing corticosteroids. Such an observation should be corroborated with appropriate diagnostic patch testing.

If concomitant skin infections are present or develop, an appropriate antifungal or antibacterial agent should be used. If a favorable response does not occur promptly, use of Desonide Ointment, 0.05% should be discontinued until the infection has been adequately controlled.

Desonide Ointment, 0.05% should not be used in the presence of infection at the treatment site, hypersensitivity to corticosteroids, or pre-existing skin atrophy.

Desonide Ointment, 0.05% should not be used in the eyes.

FOR EXTERNAL USE ONLY.

Information for Patients

Patients using topical corticosteroids should receive the following information and instructions:

1. This medication is to be used as directed by the physician. It is for external use only. Avoid contact with the eyes.
2. This medication should not be used for any disorder other than that for which it was prescribed.
3. The treated skin area should not be bandaged, otherwise covered or wrapped, so as to be occlusive unless directed by the physician.
4. Patients should report to their physician any signs of local adverse reactions.

Laboratory Tests -

The following tests may be helpful in evaluating patients for HPA axis suppression:

ACTH stimulation test
A.M. plasma cortisol test
Urinary free cortisol test

Carcinogenesis, Mutagenesis, Impairment of Fertility -

Long-term animal studies have not been performed to evaluate the carcinogenic, mutagenic, or fertility impairment potential of Desonide Ointment, 0.05%.

Pregnancy:

Teratogenic Effects:

Pregnancy Category C -

Corticosteroids have been shown to be teratogenic in laboratory animals when administered systemically at relatively low dosage levels. Some corticosteroids have been shown to be teratogenic after dermal application in laboratory animals. Animal reproductive studies have not been conducted with Desonide Ointment, 0.05%. It is also not known whether Desonide Ointment, 0.05% can cause fetal harm when administered to a pregnant woman or can affect reproduction capacity. There are no adequate and well-controlled studies in pregnant women. Desonide Ointment, 0.05% should be used during pregnancy only if the potential benefit justifies the potential risk to the fetus.

Nursing Mothers -

Systemically administered corticosteroids appear in human milk and could suppress growth, interfere with endogenous corticosteroid production, or cause other untoward effects. It is not known whether topical administration of corticosteroids could result in sufficient systemic absorption to produce detectable quantities in human milk. Because many drugs are excreted in human milk, caution should be exercised when Desonide Ointment, 0.05% is administered to a nursing woman.

Pediatric Use -

Safety and effectiveness in pediatric patients have not been established. Because of a higher ratio of skin surface area to body mass, pediatric patients are at a greater risk than adults of HPA axis suppression and Cushing’s syndrome when they are treated with topical corticosteroids. They are therefore also at greater risk of adrenal insufficiency during or after withdrawal of treatment.

Adverse effects including striae have been reported with inappropriate use of topical corticosteroids in infants and children.

HPA axis suppression, Cushing’s syndrome, linear growth retardation, delayed weight gain and intracranial hypertension have been reported in children receiving topical corticosteroids. Manifestations of adrenal suppression in children include low plasma cortisol levels and absence of response to ACTH stimulation. Manifestations of intracranial hypertension include bulging fontanelles, headaches, and bilateral papilledema.

ADVERSE REACTIONS

In controlled clinical trials, the total incidence of adverse reactions associated with the use of Desonide Ointment, 0.05% was approximately 6%. These adverse reactions were erythema, induration, pruritus, irritation, oiliness, and peripheral edema.

The following additional local adverse reactions have been reported infrequently with topical corticosteroids, and they may occur more frequently with the use of occlusive dressings and higher potency corticosteroids. These reactions are listed in approximate decreasing order of occurrence: dryness, folliculitis, acneiform eruptions, perioral dermatitis, allergic contact dermatitis, secondary infection, skin atrophy, striae, miliaria, burning and hypopigmentation.

OVERDOSAGE

Topically applied Desonide Ointment, 0.05% can be absorbed in sufficient amounts to produce systemic effects (see PRECAUTIONS).

DOSAGE AND ADMINISTRATION

Desonide Ointment, 0.05% should be applied to the affected area as a thin film from two to four times daily depending on the severity of the condition.

As with other corticosteroids, therapy should be discontinued when control is achieved. If no improvement is seen within two weeks, reassessment of diagnosis may be necessary.

Desonide Ointment, 0.05% should not be used with occlusive dressings.

HOW SUPPLIED

Desonide Ointment, 0.05% is available as follows:

15 g tube (NDC 45802-423-35)

60 g tube (NDC 45802-423-37)

STORAGE

Store at 20-25°C (68-77°F) [see USP Controlled Room Temperature].

Manufactured By Padagis

Yeruham, Israel

Distributed By Padagis

Allegan, MI 49010 • www.padagis.com

Rev 12-22

83P00 RC J1

PRINCIPAL DISPLAY PANEL - Carton

NDC 45802-423-35

Rx Only

Desonide Ointment, 0.05%

NET WT 15 g

The following image is a placeholder representing the product identifier that is either affixed or imprinted on the drug package label during the packaging operation.